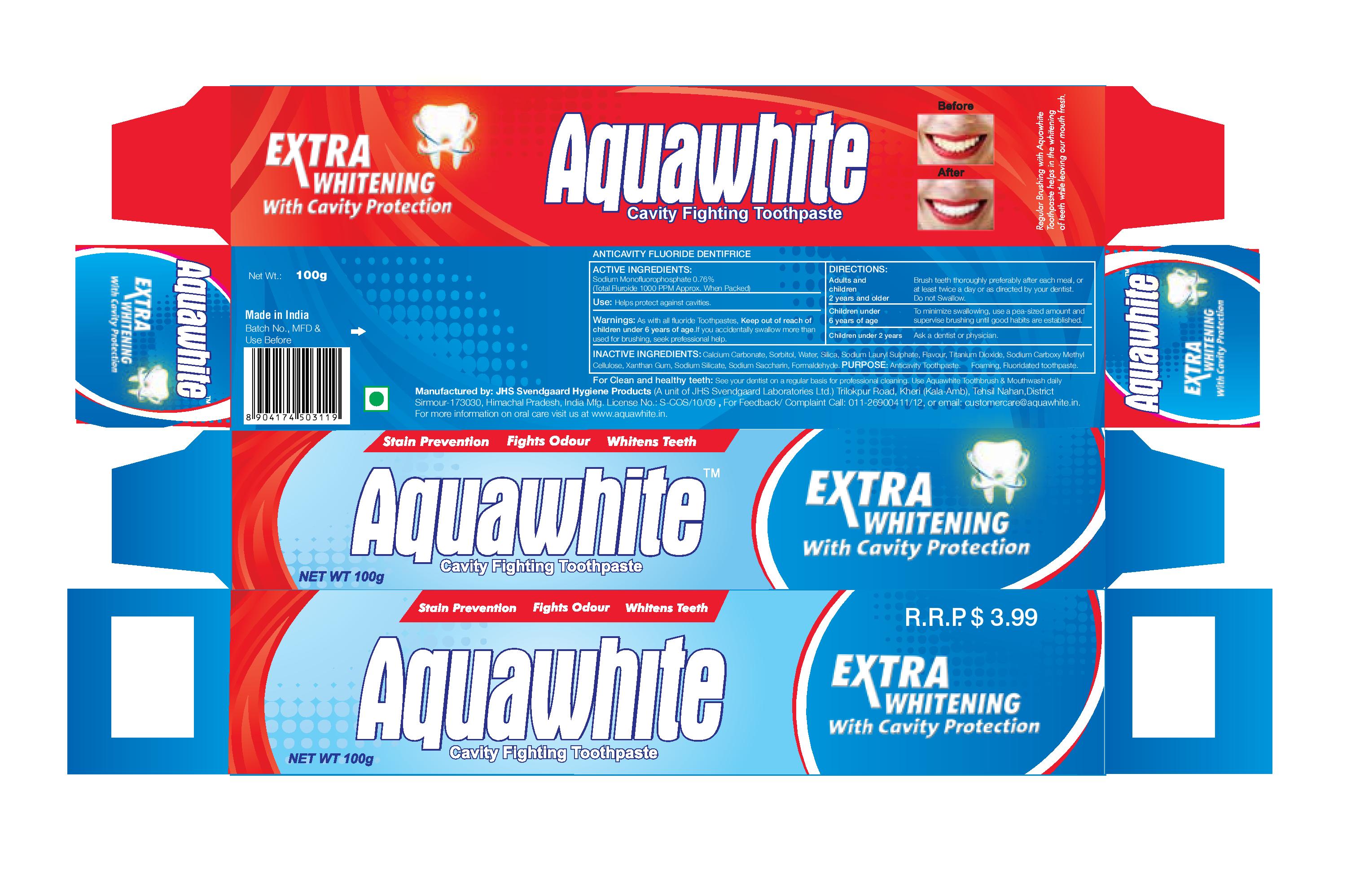 DRUG LABEL: AquaWhite Cavity FightingTooth
NDC: 72025-001 | Form: PASTE, DENTIFRICE
Manufacturer: JHS SVENDGAARD LABORATORIES LIMITED
Category: otc | Type: HUMAN OTC DRUG LABEL
Date: 20180122

ACTIVE INGREDIENTS: SODIUM MONOFLUOROPHOSPHATE 0.1 g/100 g
INACTIVE INGREDIENTS: WATER; SORBITOL; SODIUM LAURYL SULFATE; CARBOXYMETHYLCELLULOSE SODIUM; SODIUM SILICATE; XANTHAN GUM; TITANIUM DIOXIDE; SACCHARIN SODIUM

Active Ingredient

Sodium Monofluorophosphate 0.76%

Purpose:

Anticavity

Uses:

Helps protect against cavities

Warnings:

If you accidentally swallow more than used for brushing, seek professional help

Keep out of reach of children under 6 years of age

Directions:

- Adults and children 2 years and older:
- Brush teeth thoroughly after meals or at least twice a day or use as directed by a dentist.
- Do not swallow
- Children under 6 Years of Age

- To minimize swallowing use a pea-sized amount and supervise children's brushing untill good habits are established.

Children under 2 years of age:

- Ask a dentist or physician

Inactive Ingredients:

Caldium Carbonate, Sorbitor, Water, Silica, Sodium Lauryl Suphate, Titanium Dioxide, Flavor, Sodium Carboxymethylcellulose, Sodium Silicate, Xanthan Gum, Sodium Saccharin, Formaldehyde